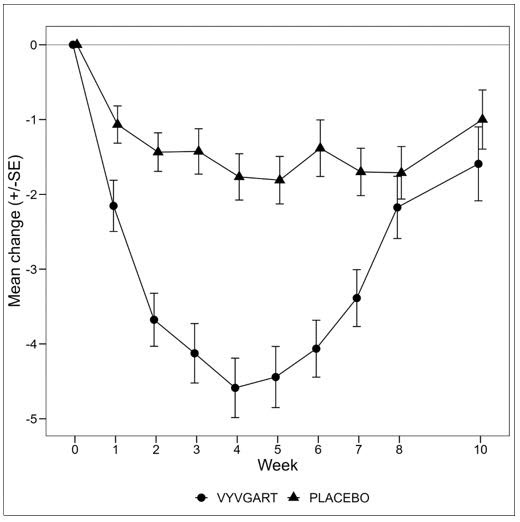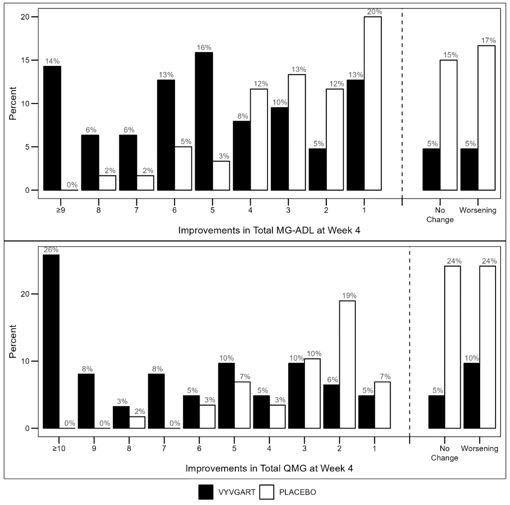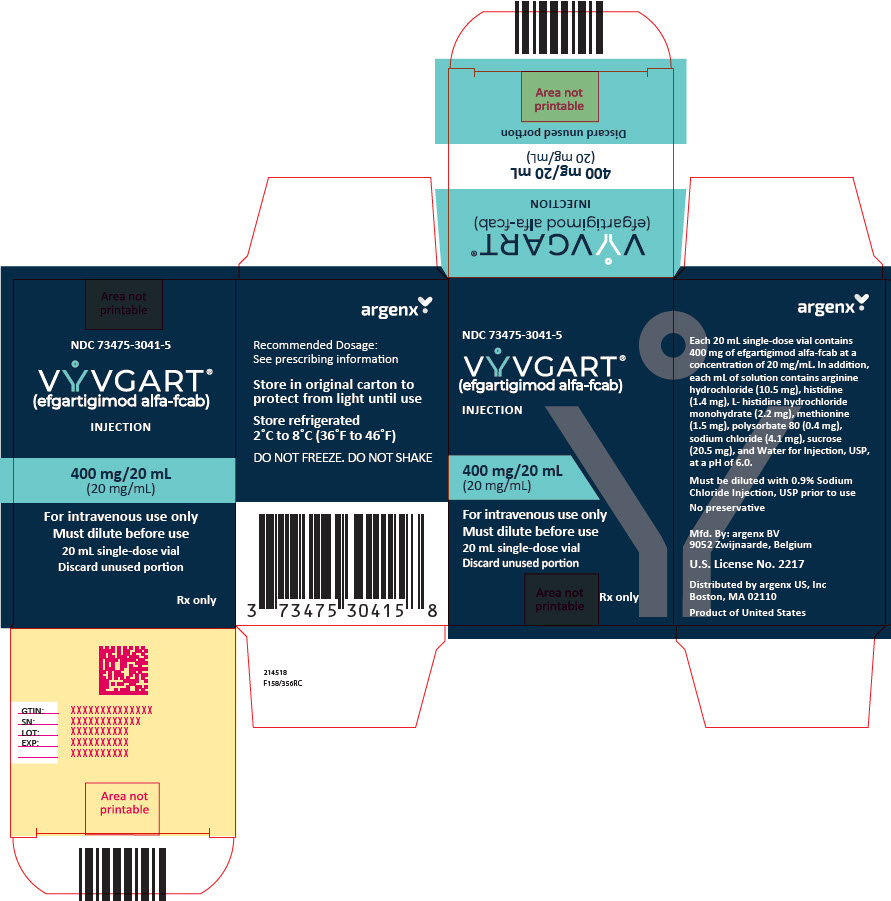 DRUG LABEL: VYVGART
NDC: 73475-3041 | Form: INJECTION
Manufacturer: argenx US
Category: prescription | Type: HUMAN PRESCRIPTION DRUG LABEL
Date: 20251021

ACTIVE INGREDIENTS: EFGARTIGIMOD ALFA 20 mg/1 mL
INACTIVE INGREDIENTS: ARGININE HYDROCHLORIDE; POLYSORBATE 80; SODIUM CHLORIDE; HISTIDINE; HISTIDINE HYDROCHLORIDE; METHIONINE; SUCROSE; WATER

HIGHLIGHTS OF PRESCRIBING INFORMATION

These highlights do not include all the information needed to use VYVGART safely and effectively. See full prescribing information for VYVGART.
VYVGART® (efgartigimod alfa-fcab) injection, for intravenous use
Initial U.S. Approval: 2021

RECENT MAJOR CHANGES

Dosage and Administration (2.2) | 10/2025

1 INDICATIONS AND USAGE

VYVGART is a neonatal Fc receptor blocker indicated for the treatment of generalized myasthenia gravis (gMG) in adult patients who are anti-acetylcholine receptor (AChR) antibody positive. (1)

2 DOSAGE AND ADMINISTRATION

- Evaluate the need to administer age-appropriate vaccines according to immunization guidelines before initiation of a new treatment cycle with VYVGART. (2.1)
- The recommended dosage is 10 mg/kg administered as an intravenous infusion over one hour once weekly for 4 weeks. In patients weighing 120 kg or more, the recommended dose is 1200 mg per infusion. (2.2)
- Administer subsequent treatment cycles based on clinical evaluation. (2.2)
- Must be diluted with 0.9% Sodium Chloride Injection, USP prior to administration. (2.3)
- Administer as an intravenous infusion over one hour via a 0.2 micron in-line filter. (2.3)

3 DOSAGE FORMS AND STRENGTHS

Injection: 400 mg in 20 mL (20 mg/mL) single-dose vial. (3)

4 CONTRAINDICATIONS

VYVGART is contraindicated in patients with serious hypersensitivity to efgartigimod alfa products or to any of the excipients of VYVGART. (4)

5 WARNINGS AND PRECAUTIONS

- Infections: Delay administration of VYVGART to patients with an active infection. Monitor for signs and symptoms of infection in patients treated with VYVGART. If serious infection occurs, administer appropriate treatment and consider withholding VYVGART until the infection has resolved. (5.1)
- Hypersensitivity Reactions: Anaphylaxis, hypotension leading to syncope, angioedema, dyspnea, and rash have occurred. If a hypersensitivity reaction occurs, the healthcare professional should institute appropriate measures if needed or the patient should seek medical attention.(4, 5.2)
- Infusion-Related Reactions: If a severe infusion-related reaction occurs, discontinue the infusion and initiate appropriate therapy; consider risks and benefits of readministering. If a mild to moderate infusion-related reaction occurs, may rechallenge with close clinical observation, slower infusion rates, and pre-medications. (5.3)

6 ADVERSE REACTIONS

Most common adverse reactions (≥ 10%) in patients treated with gMG are respiratory tract infections, headache, and urinary tract infection. (6.1)

To report SUSPECTED ADVERSE REACTIONS, contact argenx at 1-833-argx411 or FDA at 1-800-FDA-1088 or www.fda.gov/medwatch.

7 DRUG INTERACTIONS

Closely monitor for reduced effectiveness of medications that bind to the human neonatal Fc receptor. When concomitant long-term use of such medications is essential for patient care, consider discontinuing VYVGART and using alternative therapies. (7)

FULL PRESCRIBING INFORMATION

1 INDICATIONS AND USAGE

VYVGART is indicated for the treatment of generalized myasthenia gravis (gMG) in adult patients who are anti-acetylcholine receptor (AChR) antibody positive.

2 DOSAGE AND ADMINISTRATION

2.1 Recommended Vaccination

Evaluate the need to administer age-appropriate vaccines according to immunization guidelines before initiation of a new treatment cycle with VYVGART. Because VYVGART causes transient reduction in IgG levels, vaccination with live vaccines is not recommended during treatment with VYVGART [see Dosage and Administration (2.2) and Warnings and Precautions (5.1)].

2.2 Recommended Dose and Dose Schedules

Dilute VYVGART prior to administration. Administer via intravenous infusion only [see Dosage and Administration (2.3)].

The recommended dosage of VYVGART is 10 mg/kg administered as an intravenous infusion over one hour once weekly for 4 weeks. In patients weighing 120 kg or more, the recommended dose of VYVGART is 1200 mg (3 vials) per infusion.

Administer subsequent treatment cycles based on clinical evaluation.

If a scheduled infusion is missed, VYVGART may be administered up to 3 days after the scheduled time point. Thereafter, resume the original dosing schedule until the treatment cycle is completed.

2.3 Preparation and Administration Instructions

Prior to administration, VYVGART single-dose vials require dilution in 0.9% Sodium Chloride Injection, USP, to make a total volume to be administered of 125 mL (see Preparation).

Check that the VYVGART solution is clear to slightly opalescent and colorless to slightly yellow. Parenteral drug products should be inspected visually for particulate matter and discoloration prior to administration, whenever solution and container permit. Do not use if opaque particles, discoloration, or other foreign particles are present.

Use aseptic technique when preparing the VYVGART diluted solution for intravenous infusion. Each vial is for single-dose only.

Discard any unused portion.

Preparation

- Calculate the dose (mg), total drug volume (mL) of VYVGART solution required, and the number of vials needed based on the recommended dose according to the patient's body weight [see Dosage and Administration (2.2)]. Each vial contains a total of 400 mg of VYVGART at a concentration of 20 mg per mL.
- Gently withdraw the calculated dose of VYVGART from the vial(s) with a sterile syringe and needle. Discard any unused portion of the vials.
- Dilute the withdrawn VYVGART with 0.9% Sodium Chloride Injection, USP to make a total volume of 125 mL for intravenous infusion.
- Gently invert the infusion bag containing the diluted VYVGART without shaking to ensure thorough mixing of the product and the diluent.
- The diluted solution can be administered using polyethylene (PE), polyvinyl chloride (PVC), ethylene vinyl acetate (EVA), or ethylene/polypropylene copolymer bags (polyolefins bags), and with PE, PVC, EVA, or polyurethane/polypropylene infusion lines.

Storage Conditions of the Diluted Solution

- VYVGART does not contain preservatives. Administer immediately after dilution and complete the infusion within 4 hours of dilution.
- If immediate use is not possible, the diluted solution may be stored refrigerated at 2°C to 8°C (36°F to 46°F) for up to 8 hours. Do not freeze. Protect from light. Allow the diluted drug to reach room temperature before administration. Complete the infusion within 4 hours of removal from the refrigerator. Do not heat the diluted drug in any manner other than via ambient air.

Administration

- VYVGART should be administered via intravenous infusion by a healthcare professional.
- Visually inspect VYVGART diluted solution for particles or discoloration prior to administration. Do not use if it is discolored, or if opaque or foreign particles are seen.
- Infuse the total 125 mL of diluted solution intravenously over one hour via a 0.2 micron in-line filter.
- After administration of VYVGART, flush the entire line with 0.9% Sodium Chloride Injection, USP.
- Monitor patients during administration and for 1 hour thereafter for clinical signs and symptoms of hypersensitivity reactions. If a hypersensitivity reaction occurs during administration, discontinue administration of VYVGART and institute appropriate supportive measures [see Warnings and Precautions (5.2)].
- Other medications should not be injected into infusion side ports or mixed with VYVGART.

3 DOSAGE FORMS AND STRENGTHS

Injection: 400 mg/20 mL (20 mg/mL) as a colorless to slightly yellow, clear to slightly opalescent solution, in a single-dose vial.

4 CONTRAINDICATIONS

VYVGART is contraindicated in patients with serious hypersensitivity to efgartigimod alfa products or to any of the excipients of VYVGART. Reactions have included anaphylaxis and hypotension leading to syncope [see Warnings and Precautions (5.2)].

5 WARNINGS AND PRECAUTIONS

5.1 Infections

VYVGART may increase the risk of infection. The most common infections observed in Study 1 were urinary tract infection (10% of VYVGART-treated patients compared to 5% of placebo-treated patients) and respiratory tract infections (33% of VYVGART-treated patients compared to 29% of placebo-treated patients) [see Adverse Reactions (6.1) and Clinical Studies (14)]. A higher frequency of patients who received VYVGART compared to placebo were observed to have below normal levels for white blood cell counts (12% versus 5%, respectively), lymphocyte counts (28% versus 19%, respectively), and neutrophil counts (13% versus 6%, respectively). The majority of infections and hematologic abnormalities were mild to moderate in severity. Delay VYVGART administration in patients with an active infection until the infection is resolved. During treatment with VYVGART, monitor for clinical signs and symptoms of infections. If serious infection occurs, administer appropriate treatment and consider withholding VYVGART until the infection has resolved.

Immunization

Evaluate the need to administer age-appropriate vaccines according to immunization guidelines before initiation of a new treatment cycle with VYVGART. The safety of immunization with live vaccines and the immune response to vaccination during treatment with VYVGART are unknown. Because VYVGART causes a reduction in IgG levels, vaccination with live vaccines is not recommended during treatment with VYVGART.

5.2 Hypersensitivity Reactions

In clinical trials, hypersensitivity reactions, including rash, angioedema, and dyspnea were observed in VYVGART-treated patients. Hypersensitivity reactions were mild or moderate, occurred within one hour to three weeks of administration, and did not lead to treatment discontinuation.

Anaphylaxis and hypotension leading to syncope have been reported in postmarketing experience with VYVGART. Anaphylaxis and hypotension occurred during or within an hour of administration and led to infusion discontinuation and in some cases to permanent treatment discontinuation.

Monitor patients during administration and for 1 hour thereafter for clinical signs and symptoms of hypersensitivity reactions. If a hypersensitivity reaction occurs, the healthcare professional should institute appropriate measures if needed or the patient should seek medical attention. VYVGART is contraindicated in patients with a history of serious hypersensitivity to efgartigimod alfa products or to any of the excipients of VYVGART [see Contraindications (4)].

5.3 Infusion-Related Reactions

Infusion-related reactions have been reported with VYVGART in postmarketing experience. The most frequent symptoms and signs were hypertension, chills, shivering, and thoracic, abdominal, and back pain. Infusion-related reactions occurred during or within an hour of administration and led to infusion discontinuation. If a severe infusion-related reaction occurs during administration, discontinue VYVGART infusion and initiate appropriate therapy. Consider the risks and benefits of readministering VYVGART following a severe infusion-related reaction. If a mild to moderate infusion-related reaction occurs, patients may be rechallenged with close clinical observation, slower infusion rates, and pre-medications.

6 ADVERSE REACTIONS

The following clinically significant adverse reactions are described elsewhere in the labeling:

- Infections [see Warnings and Precautions (5.1)]
- Hypersensitivity Reactions [see Warnings and Precautions (5.2)]
- Infusion-Related Reactions [see Warnings and Precautions (5.3)]

6.1 Clinical Trials Experience

Because clinical trials are conducted under widely varying conditions, adverse reaction rates observed in the clinical trials of a drug cannot be directly compared to rates in the clinical trials of another drug and may not reflect the rates observed in practice.

In clinical studies, the safety of VYVGART has been evaluated in 246 patients who received at least one dose of VYVGART, including 57 patients exposed to at least 7 treatment cycles and 8 patients exposed to at least 10 treatment cycles.

In a placebo-controlled study (Study 1) in patients with gMG, 84 patients received VYVGART 10 mg/kg [see Clinical Studies (14)]. Of these 84 patients, approximately 75% were female, 82% were White, 11% were Asian, and 8% were of Hispanic or Latino ethnicity. The mean age at study entry was 46 years (range 19 to 78).

The minimum time to initiate a subsequent cycle, specified by study protocol, was 28 days from the last administration of the previous treatment cycle. On average, VYVGART-treated patients received 2 cycles in Study 1. The mean and median times to the second treatment cycle were 54 days and 50 days from the last administration of the first treatment cycle, respectively, for VYVGART-treated patients.

Adverse reactions reported in at least 5% of patients treated with VYVGART and more frequently than placebo are summarized in Table 1. The most common adverse reactions (reported in at least 10% of VYVGART-treated patients) were respiratory tract infection, headache, and urinary tract infection.

Table 1: Adverse Reactions in ≥ 5% of Patients Treated with VYVGART and More Frequently than in Placebo-Treated Patients in Study 1 (Safety Population)
Adverse reaction | VYVGART (N=84) % | Placebo (N=83) %
Respiratory tract infection | 33 | 29
Headache [Headache includes migraine and procedural headache.] | 32 | 29
Urinary tract infection | 10 | 5
Paraesthesia [Paraesthesia includes oral hypoesthesia, hypoesthesia, and hyperesthesia.] | 7 | 5
Myalgia | 6 | 1

The safety of initiating subsequent cycles between 7 and 28 days from the last administration of the previous treatment cycle was assessed in 60 patients. Of these patients, 63% were exposed to treatment for over a year when cycles were initiated less than 4 weeks after the last administration. Safety in these patients was similar to that seen in Study 1.

6.2 Postmarketing Experience

The following adverse reactions have been identified during postapproval use of VYVGART. Because these reactions are reported voluntarily from a population of uncertain size, it is not always possible to reliably estimate their frequency or establish a causal relationship to drug exposure.

Immune System Disorders: Hypersensitivity reactions including anaphylaxis and hypotension, and infusion-related reactions [see Warnings and Precautions (5.2, 5.3)].

6.3 Immunogenicity

As with all therapeutic proteins, there is potential for immunogenicity. The detection of antibody formation is highly dependent on the sensitivity and specificity of the assay. Additionally, the observed incidence of antibody (including neutralizing antibody) positivity in an assay may be influenced by several factors including assay methodology, sample handling, timing of sample collection, concomitant medications, and underlying disease. For these reasons, comparison of the incidence of antibodies to VYVGART in the studies described below with the incidence of antibodies in other studies or to other products may be misleading.

In up to 26 weeks of treatment in Study 1, 20% (17/83) of patients developed antibodies to VYVGART. Seven percent (6/83) of patients developed neutralizing antibodies.

Because few patients tested positive for anti-efgartigimod alfa-fcab antibodies and neutralizing antibodies, the available data are too limited to make definitive conclusions regarding immunogenicity and the effect on pharmacokinetics, safety, or efficacy of VYVGART.

7 DRUG INTERACTIONS

7.1 Effect of VYVGART on Other Drugs

Concomitant use of VYVGART with medications that bind to the human neonatal Fc receptor (FcRn) (e.g., immunoglobulin products, monoclonal antibodies, or antibody derivates containing the human Fc domain of the IgG subclass) may lower systemic exposures and reduce effectiveness of such medications. Closely monitor for reduced effectiveness of medications that bind to the human neonatal Fc receptor. When concomitant long-term use of such medications is essential for patient care, consider discontinuing VYVGART and using alternative therapies.

8 USE IN SPECIFIC POPULATIONS

8.1 Pregnancy

Pregnancy Exposure Registry

There is a pregnancy exposure registry that monitors pregnancy outcomes in women exposed to VYVGART during pregnancy. Healthcare providers and patients may call 1-855-272-6524 or go to https://www.Vyvgartpregnancy.com to enroll in or to obtain information about the registry.

Risk Summary

There are no available data on the use of VYVGART during pregnancy. There is no evidence of adverse developmental outcomes following the administration of VYVGART at up to 100 mg/kg/day in rats and rabbits (see Data).

The background rate of major birth defects and miscarriage in the indicated population is unknown. In the U.S. general population, the estimated background rate of major birth defects and miscarriage in clinically recognized pregnancies is 2% to 4% and 15% to 20%, respectively.

Clinical Considerations

Fetal/Neonatal Adverse Reactions

Monoclonal antibodies are increasingly transported across the placenta as pregnancy progresses, with the largest amount transferred during the third trimester. Therefore, efgartigimod alfa-fcab may be transmitted from the mother to the developing fetus.

As VYVGART is expected to reduce maternal IgG antibody levels, reduction in passive protection to the newborn is anticipated. Risk and benefits should be considered prior to administering live vaccines to infants exposed to VYVGART in utero [see Warnings and Precautions (5.1)].

Data

Animal Data

Intravenous administration of efgartigimod alfa-fcab (0, 30, or 100 mg/kg/day) to pregnant rats and rabbits throughout organogenesis resulted in no adverse effects on embryofetal development in either species. The doses tested are 3 and 10 times the recommended human dose (RHD) of 10 mg/kg, on a body weight (mg/kg) basis.

Intravenous administration of efgartigimod alfa-fcab (0, 30, or 100 mg/kg/day) to rats throughout gestation and lactation resulted in no adverse effects on pre- or postnatal development. The doses tested are 3 and 10 times the recommended human dose (RHD) of 10 mg/kg, on a body weight (mg/kg) basis.

8.2 Lactation

Risk Summary

There is no information regarding the presence of efgartigimod alfa-fcab in human milk, the effects on the breastfed infant, or the effects on milk production. Maternal IgG is known to be present in human milk.

The developmental and health benefits of breastfeeding should be considered along with the mother's clinical need for VYVGART and any potential adverse effects on the breastfed infant from VYVGART or from the underlying maternal condition.

8.4 Pediatric Use

Safety and effectiveness in pediatric patients have not been established.

8.5 Geriatric Use

Clinical studies of VYVGART did not include sufficient numbers of patients aged 65 and older to determine whether they respond differently from younger adult patients.

8.6 Renal Impairment

No dose adjustment of VYVGART is needed for patients with mild renal impairment. There are insufficient data to evaluate the impact of moderate renal impairment (eGFR 30-59 mL/min/1.73 m^2) and severe renal impairment (eGFR <30 mL/min/1.73 m^2) on pharmacokinetic parameters of efgartigimod alfa-fcab [see Clinical Pharmacology (12.3)].

11 DESCRIPTION

Efgartigimod alfa-fcab is a human immunoglobulin G1 (IgG1) -derived Fc fragment (fragment, crystallized) of the za allotype. The efgartigimod alfa-fcab Fc fragment is a homodimer consisting of two identical peptide chains each consisting of 227 amino acids linked together by two interchain disulfide bonds with affinity for FcRn. The molecular weight of efgartigimod alfa-fcab is approximately 54 kDa.

VYVGART (efgartigimod alfa-fcab) injection is a sterile, preservative free, clear to slightly opalescent, colorless to slightly yellow solution supplied in a single-dose vial for infusion after dilution.

Each 20 mL single-dose vial contains 400 mg of efgartigimod alfa-fcab at a concentration of 20 mg/mL. In addition, each mL of solution contains arginine hydrochloride (10.5 mg), histidine (1.4 mg), L- histidine hydrochloride monohydrate (2.2 mg), methionine (1.5 mg), polysorbate 80 (0.4 mg), sodium chloride (4.1 mg), sucrose (20.5 mg), and Water for Injection, USP, at a pH of 6.0.

12 CLINICAL PHARMACOLOGY

12.1 Mechanism of Action

Efgartigimod alfa-fcab is a human IgG1 antibody fragment that binds to the neonatal Fc receptor (FcRn), resulting in the reduction of circulating IgG.

12.2 Pharmacodynamics

In Study 1 [see Clinical Studies (14)], the pharmacological effect of efgartigimod alfa-fcab was assessed by measuring the decrease in serum IgG levels and AChR autoantibody levels. In patients testing positive for AChR antibodies and who were treated with VYVGART, there was a reduction in total IgG levels relative to baseline. Decrease in AChR autoantibody levels followed a similar pattern.

12.3 Pharmacokinetics

Efgartigimod alfa-fcab exhibits linear pharmacokinetics, and following single doses of efgartigimod alfa-fcab, exposures increase proportionally up to 50 mg/kg (5 times the recommended dosage).

Distribution

The volume of distribution is 15 to 20L.

Metabolism and Elimination

Efgartigimod alfa-fcab is expected to be degraded by proteolytic enzymes into small peptides and amino acids.

The terminal half-life is 80 to 120 hours (3 to 5 days).

After a single intravenous dose of 10 mg/kg efgartigimod alfa-fcab in healthy subjects, less than 0.1% of the administered dose was recovered in urine.

Specific Populations

Age, Sex, and Race

A population pharmacokinetics analysis assessing the effects of age, sex, and race did not suggest any clinically significant impact of these covariates on efgartigimod alfa-fcab exposures.

Patients with Renal Impairment

No dedicated pharmacokinetic study has been performed in patients with renal impairment.

A population PK analysis of data from the VYVGART clinical studies indicated that patients with mild renal impairment (eGFR 60-89 mL/min/1.72m²) had 22% increase in exposure relative to the exposure in patients with normal renal function [see Use in Specific Populations (8.6)].

Patients with Hepatic Impairment

No dedicated pharmacokinetic study has been performed in patients with hepatic impairment. Hepatic impairment is not expected to affect the pharmacokinetics of efgartigimod alfa-fcab.

Drug Interaction Studies

Clinical drug interactions studies have not been performed with efgartigimod alfa-fcab.

P450 Enzymes

Efgartigimod alfa-fcab is not metabolized by cytochrome P450 enzymes; therefore, interactions with concomitant medications that are substrates, inducers, or inhibitors of cytochrome P450 enzymes are unlikely.

Drug Interactions with Other Drugs or Biological Products

Efgartigimod alfa-fcab may decrease concentrations of compounds that bind to the human FcRn [see Drug Interactions (7.1)].

13 NONCLINICAL TOXICOLOGY

13.1 Carcinogenesis, Mutagenesis, Impairment of Fertility

Carcinogenesis and Mutagenesis

No studies have been conducted to assess the carcinogenic potential of efgartigimod alfa-fcab.

No studies have been conducted to assess the genotoxic potential of efgartigimod alfa-fcab.

Impairment of Fertility

Intravenous administration of efgartigimod alfa-fcab (0, 30, or 100 mg/kg/day) to male and female rats prior to and during mating and continuing in females through gestation day 7 resulted in no adverse effects on fertility. The doses tested are 3 and 10 times the recommended human dose (RHD) of 10 mg/kg, on a body weight (mg/kg) basis.

14 CLINICAL STUDIES

The efficacy of VYVGART for the treatment of generalized myasthenia gravis (gMG) in adults who are AChR antibody positive was established in a 26-week, multicenter, randomized, double-blind, placebo-controlled trial (Study 1; NCT03669588).

Study 1 enrolled patients who met the following criteria at screening:

1. Myasthenia Gravis Foundation of America (MGFA) clinical classification class II to IV
2. MG-Activities of Daily Living (MG-ADL) total score of ≥ 5
3. On stable dose of MG therapy prior to screening, that included acetylcholinesterase (AChE) inhibitors, steroids, or non-steroidal immunosuppressive therapies (NSISTs), either in combination or alone
4. IgG levels of at least 6 g/L

A total of 167 patients were enrolled in Study 1 and were randomized to receive either VYVGART 10mg/kg (1200 mg for those weighing 120 kg or more) (n=84) or placebo (n=83). Baseline characteristics were similar between treatment groups. Patients had a median age of 46 years at screening (range: 19 to 81 years) and a median time since diagnosis of 7 years. Seventy-one percent were female, and 84% were White. Median MG-ADL total score was 9, and median Quantitative Myasthenia Gravis (QMG) total score was 16. The majority of patients (n=65 for VYVGART; n=64 for placebo) were positive for AChR antibodies.

At baseline, over 80% of patients in each group received AChE inhibitors, over 70% in each treatment group received steroids, and approximately 60% in each treatment group received NSISTs, at stable doses.

Patients were treated with VYVGART at the recommended dosage regimen [see Dosage and Administration (2.2)]. Subsequent treatment cycles were administered based on clinical evaluation, but no sooner than 28 days from the last administration of the previous treatment cycle.

The efficacy of VYVGART was measured using the Myasthenia Gravis-Specific Activities of Daily Living scale (MG-ADL) which assesses the impact of gMG on daily functions of 8 signs or symptoms that are typically affected in gMG. Each item is assessed on a 4-point scale where a score of 0 represents normal function and a score of 3 represents loss of ability to perform that function. A total score ranges from 0 to 24, with the higher scores indicating more impairment. In this study, an MG-ADL responder was defined as a patient with a 2-point or greater reduction in the total MG-ADL score compared to the treatment cycle baseline for at least 4 consecutive weeks, with the first reduction occurring no later than 1 week after the last infusion of the cycle.

The primary efficacy endpoint was the comparison of the percentage of MG-ADL responders during the first treatment cycle between treatment groups in the AChR-Ab positive population. A statistically significant difference favoring VYVGART was observed in the MG-ADL responder rate during the first treatment cycle [67.7% in the VYVGART-treated group vs 29.7% in the placebo-treated group (p <0.0001)].

The efficacy of VYVGART was also measured using the Quantitative Myasthenia Gravis (QMG) total score which is a 13-item categorical grading system that assesses muscle weakness. Each item is assessed on a 4-point scale where a score of 0 represents no weakness and a score of 3 represents severe weakness. A total possible score ranges from 0 to 39, where higher scores indicate more severe impairment. In this study, a QMG responder was defined as a patient who had a 3-point or greater reduction in the total QMG score compared to the treatment cycle baseline for at least 4 consecutive weeks, with the first reduction occurring no later than 1 week after last infusion of the cycle.

The secondary endpoint was the comparison of the percentage of QMG responders during the first treatment cycle between both treatment groups in the AChR-Ab positive patients. A statistically significant difference favoring VYVGART was observed in the QMG responder rate during the first treatment cycle [63.1% in the VYVGART-treated group vs 14.1% in the placebo-treated group (p <0.0001)].

The results are presented in Table 2.

Table 2: MG-ADL and QMG Responders During Cycle 1 in AChR-Ab Positive Patients (mITT Analysis Set)
 | VYVGART n=65 % | Placebo n=64 % | P-value | Odds Ratio (95% CI)
MG-ADL Responders | 67.7 | 29.7 | < 0.0001 | 4.951 (2.213, 11.528)
QMG Responders | 63.1 | 14.1 | < 0.0001 | 10.842 (4.179, 31.200)
MG-ADL=Myasthenia Gravis Activities of Daily Living; QMG =Quantitative Myasthenia Gravis; mITT=modified intent-to-treat; n=number of patients for whom the observation was reported; CI = confidence interval;
Logistic regression stratified for AChR-Ab status (if applicable), Japanese/Non-Japanese and standard of care, with baseline MG-ADL as covariate / QMG as covariates
Two-sided exact p-value

Figure 1 shows the mean change from baseline on the MG-ADL during cycle 1.

Figure 1: Mean Change in Total MG-ADL From Cycle 1 Baseline Over Time in AChR-Ab Positive Patients (mITT Analysis Set)

Figure 2 shows the distribution of response on the MG-ADL and QMG during cycle 1, four weeks after the first infusion with VYVGART.

Figure 2: Percentage of Patients with MG-ADL and QMG Total Score Change 4 Weeks Post Initial Infusion of the First Cycle in AChR-Ab Positive Population

16 HOW SUPPLIED/STORAGE AND HANDLING

VYVGART (efgartigimod alfa-fcab) injection is a preservative free, sterile, colorless to slightly yellow, clear to slightly opalescent solution supplied as 400 mg/20 mL (20 mg/mL) in one single-dose vial per carton (NDC 73475-3041-5).

STORAGE AND HANDLING

Store VYVGART vials refrigerated at 2°C to 8°C (36°F to 46°F) in the original carton to protect from light until time of use. Do not freeze. Do not shake.

Refer to Dosage and Administration (2.3) for information on stability and storage of the diluted solutions of VYVGART.

17 PATIENT COUNSELING INFORMATION

Infections

Instruct patients to communicate any history of infections to the healthcare provider and to contact their healthcare provider if they develop any symptoms of an infection. Advise patients to complete age-appropriate vaccines according to immunization guidelines prior to initiation of a new treatment cycle with VYVGART. Administration of live vaccines is not recommended during treatment with VYVGART [see Warnings and Precautions (5.1)].

Hypersensitivity Reactions

Inform patients that hypersensitivity reactions, including angioedema and anaphylaxis, have occurred in patients who were treated with VYVGART. Inform patients about the signs and symptoms of these reactions, and advise patients to contact their healthcare provider immediately if these occur [see Warnings and Precautions (5.2)].

Infusion-Related Reactions

Advise patients of the potential risk of infusion-related reactions, which can include hypertension, chills, shivering, and chest, abdominal, and back pain [see Warnings and Precautions (5.3)].

Pregnancy Registry

There is a pregnancy exposure registry that monitors pregnancy outcomes in women exposed to VYVGART during pregnancy. Encourage participation and advise patients about how they may enroll in the registry [see Use In Specific Populations (8.1)].

Manufactured by:

argenx BV
Industriepark 7
9052 Zwijnaarde, Belgium

License Number 2217

Distributed by:

argenx US, Inc.
33 Arch Street
Boston, MA 02110

VYVGART is a registered trademark of argenx BV.
© 2025 argenx BV

For patent information: www.argenx.com/patents

PRINCIPAL DISPLAY PANEL - 400 mg/20 mL Vial Carton

NDC 73475-3041-5

VYVGART®
(efgartigimod alfa-fcab)
INJECTION

400 mg/20 mL
(20 mg/mL)

For intravenous use only
Must dilute before use
20 mL single-dose vial
Discard unused portion

Rx only